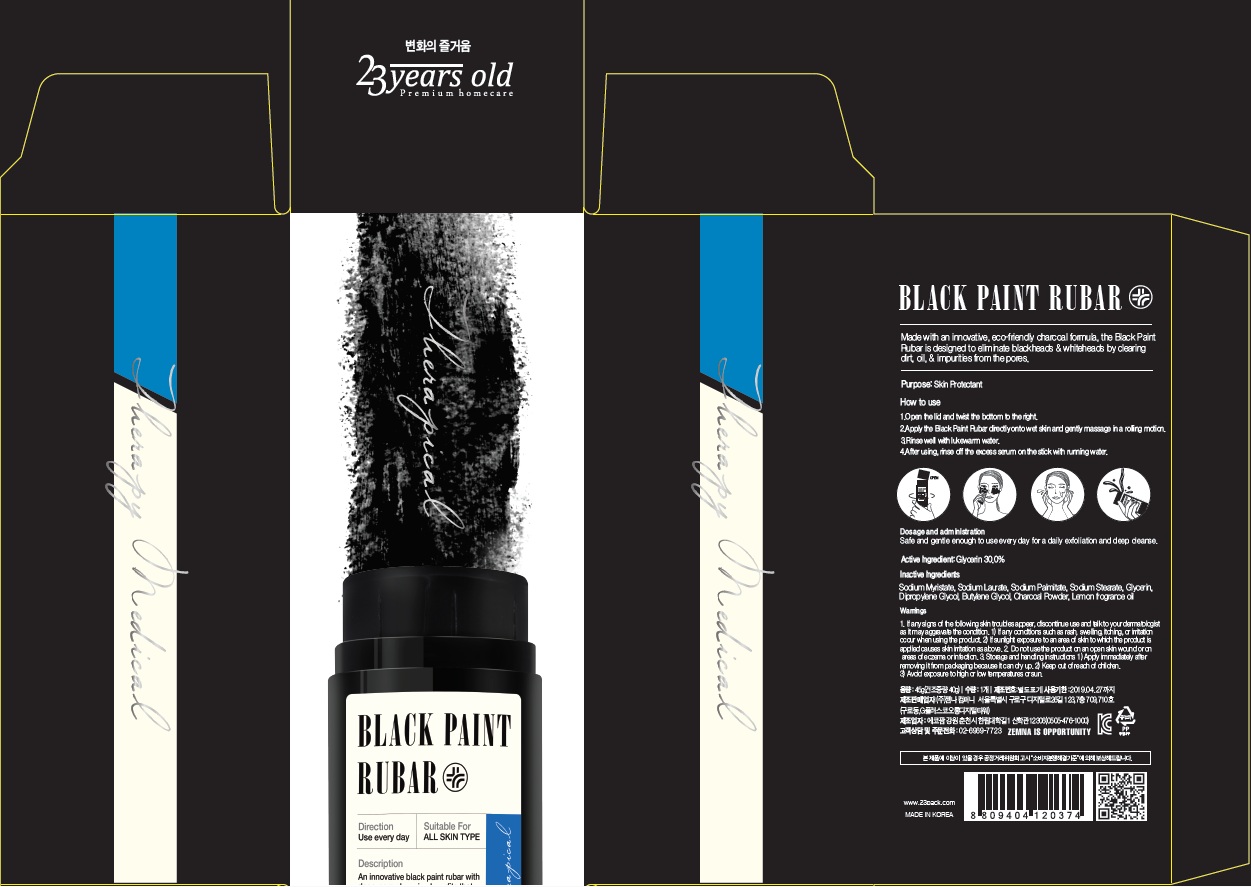 DRUG LABEL: Black Paint Rubar
NDC: 70768-020 | Form: GEL
Manufacturer: ZEMNA COMPANY CO., Ltd
Category: otc | Type: HUMAN OTC DRUG LABEL
Date: 20160719

ACTIVE INGREDIENTS: Glycerin 13.5 g/45 g
INACTIVE INGREDIENTS: Butylene Glycol; Dipropylene Glycol

ACTIVE INGREDIENT

Active Ingredient: Glycerin 30.0%

INACTIVE INGREDIENT

Inactive Ingredients: Sodium Laurate, Sodium Myristate, Butylene Glycol, Dipropylene Glycol, Sodium Stearate, Sodium Palmitate, Charcoal Powder, Fragrance

PURPOSE

Purpose: Skin Protectant

WARNINGS

Warnings: 1. If any signs of the following skin troubles appear, discontinue use and talk to your dermatologist as it may aggravate the condition. 1) If any conditions such as rash, swelling, itching, or irritation occur when using the product. 2) If sunlight exposure to an area of skin to which the product is applied causes skin irritation as above. 2. Do not use the product on an open skin wound or on areas of eczema or infection. 3. Storage and handling instructions 1) Keep out of reach of children. 2) Avoid exposure to high or low temperatures or sun.

How to use: 1) Open the lid and twist the bottom to the right. 2) Apply the Black Paint Rubar directly onto wet skin and gently massage in a rolling motion. 3) Rinse well with lukewarm water. 4) After using, rinse off the excess serum on the stick with running water.

DOSAGE & ADMINISTRATION

Dosage & Administration: Safe and gentle enough to use every day for a daily exfoliation and deep cleanse

KEEP OUT OF REACH OF CHILDREN